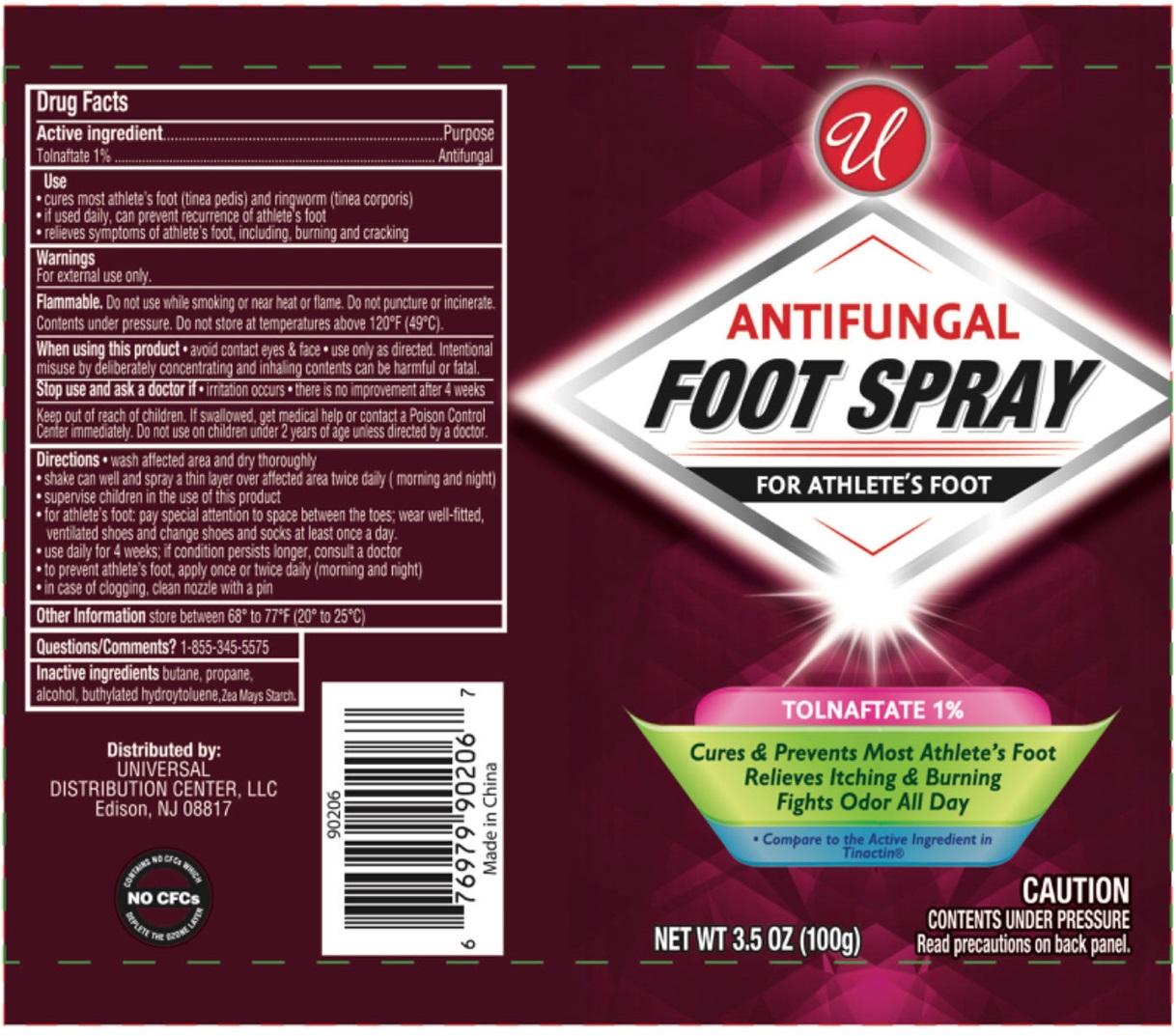 DRUG LABEL: ANTIFUNGAL FOOT
NDC: 52000-418 | Form: AEROSOL, SPRAY
Manufacturer: Universal Distribution Center LLC
Category: otc | Type: HUMAN OTC DRUG LABEL
Date: 20240716

ACTIVE INGREDIENTS: TOLNAFTATE 1 g/100 g
INACTIVE INGREDIENTS: BUTANE; PROPANE; ALCOHOL; BUTYLATED HYDROXYTOLUENE; STARCH, CORN

ANTIFUNGAL FOOT SPRAY

Active ingredient

Tolnaftate 1%

Purpose

Antifungal

Use

• cures most athlete's foot (tinea pedis) and ringworm (tinea corporis)
• if used daily, can prevent recurrence of athlete's foot
• relieves symptoms of athlete's foot, including, burning and cracking

Warnings

For external use only.

Flammable. Do not use while smoking or near heat or flame. Do not puncture or incinerate. Contents under pressure. Do not store at temperatures above 120°F (49°C).

When using this product • avoid contact eyes & face • use only as directed. Intentional misuse by deliberately concentrating and inhaling contents can be harmful or fatal.

Stop use and ask a doctor if • irritation occurs • there is no improvement after 4 weeks

Keep out of reach of children. If swallowed, get medical help or contact a Poison Control Center immediately. Do not use on children under 2 years of age unless directed by a doctor.

Directions

• wash affected area and dry thoroughly
• shake can well and spray a thin layer over affected area twice daily (morning and night)
• supervise children in the use of this product
• for athlete's foot: pay special attention to space between the toes; wear well-fitted, ventilated shoes and change shoes and socks at least once a day.
• use daily for 4 weeks; if condition persists longer, consult a doctor
• to prevent athlete's foot, apply once or twice daily (morning and night)
• in case of clogging, clean nozzle with a pin

Other Information

store between 68° to 77°F (20° to 25°C)

Questions/Comments?

1-855-345-5575

Inactive ingredients

butane, propane, alcohol, butylated hydroxytoluene, Zea Mays Starch.

FOR ATHLETE'S FOOT

Cures & Prevents Most Athlete's Foot
Relieves Itching & Burning
Fights Odor All Day

*Compare to the Active Ingredient in Tinactin®

CAUTION
CONTENTS UNDER PRESSURE
Read precautions on back panel.

Distributed by:
UNIVERSAL DISTRIBUTION CENTER, LLC
Edison, NJ 08817

NO CFCs
CONTAINS NO CFCs WHICH DEPLETE THE OZONE LAYER

Made in China